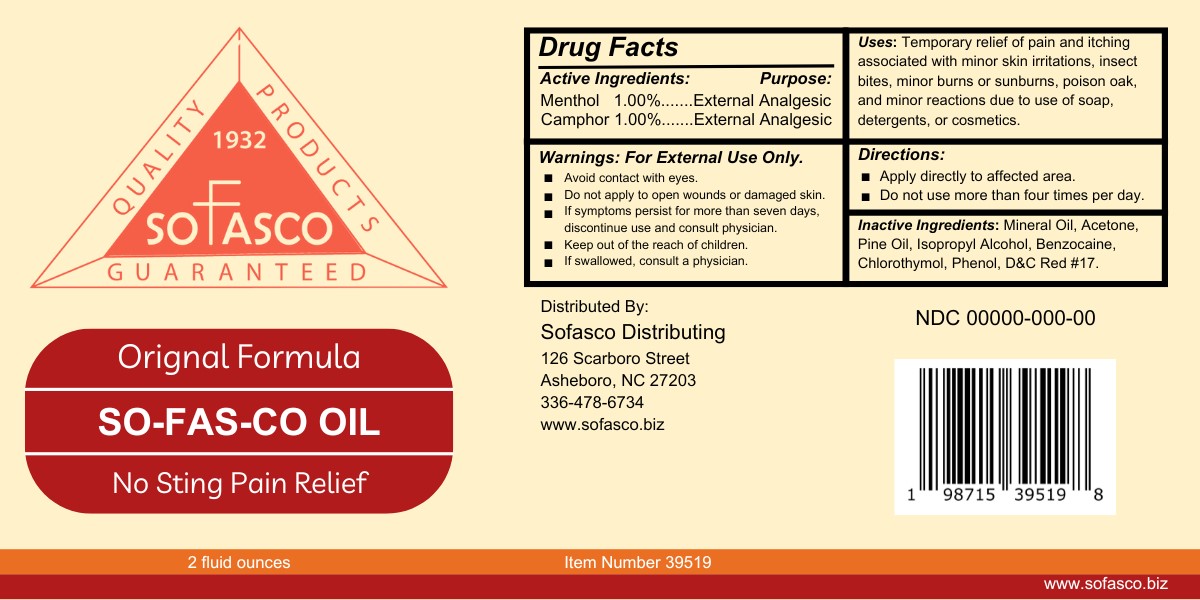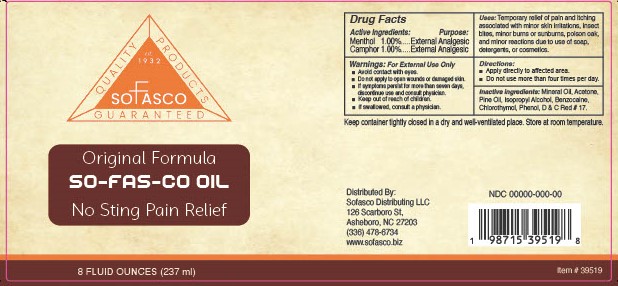 DRUG LABEL: So-fas-co oil
NDC: 74446-345 | Form: GEL
Manufacturer: INDUSTRY SUPPLY INC
Category: otc | Type: HUMAN OTC DRUG LABEL
Date: 20240826

ACTIVE INGREDIENTS: MENTHOL 1 g/100 g; CHLOROTHYMOL 0.3 g/100 g; CAMPHOR (SYNTHETIC) 1 g/100 g
INACTIVE INGREDIENTS: ISOPROPYL ALCOHOL 1.2 g/100 g; ACETONE 1.92 g/100 g; BENZOCAINE 0.3 g/100 g; MINERAL OIL 92.69 g/100 g; 2-(1-METHYLBUTYL)PHENOL 0.55 g/100 g; PINE NEEDLE OIL (PINUS SYLVESTRIS) 1.03 g/100 g; D&C RED NO. 17 0.002 g/100 g

This product is a topical analgesic. This product consists of the following active ingredients.

1. Chlorothymol (.3% v/v).
2. Camphor (1% v/v).
3. Menthol (1% v/v).

The firm does not add other active or inactive ingredients. Different or additional ingredients may impact the quality and potency of the product.

Active Ingredient(s)

Chlorothymol 3% v/v. Purpose:Antifungal

Camphor 1% v/v. Purpose:External Analgesic

Menthol 1% v/v. Purpose: External Analgesic

Purpose

Analgesic

Use

Temporary relief of pain and itching associated with minor skin irritations, insect bites, minor burns or sunburns, poison oak and minor reactions due to use of soaps, detergents or cosmetics.

Warnings

For external use only. Avoid contact with eyes. Do not apply to open wounds or damaged skin. If symptoms persist for more than seven days, discontinue use and consult physician. Keep out of reach of children, if swallowed consult a physician.

Do not use

- more than four times per day

WHEN USING

For external use only. Avoid contact with eyes. Do not apply to open wounds or damaged skin. If symptoms persist for more than seven days, discontinue use and consult physician. Keep out of reach of children, if swallowed consult a physician.

Stop use and ask a doctor if irritation or rash occurs. These may be signs of a serious condition.

Keep out of reach of children. If swallowed, get medical help or contact a Poison Control Center right away.

Directions

Apply directly to affected area

Other information

Keep container tightly closed in a dry and well-ventilated place. Store at room temperature.

Inactive ingredients

Mineral Oil, Acetone, Benzocaine, D&C Red no 17, Isopropyl Alcohol, Phenol Solution, Pine needle oil